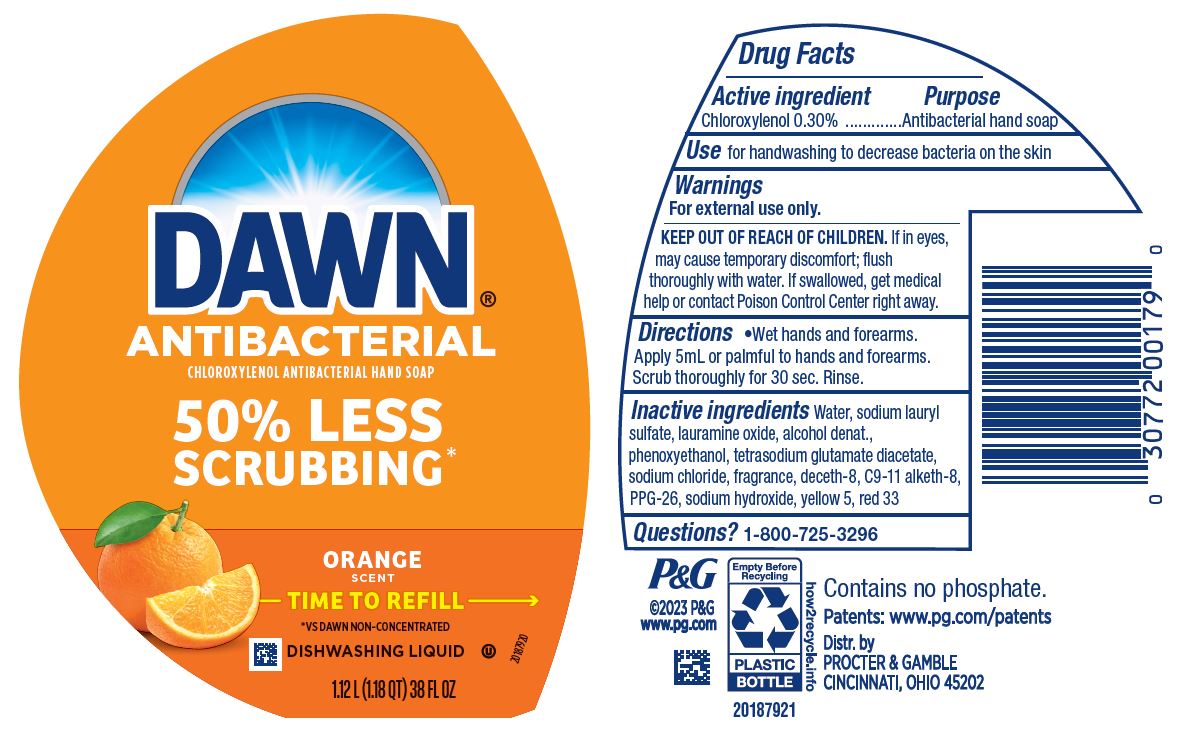 DRUG LABEL: Dawn Ultra Antibacterial Hand
NDC: 37000-617 | Form: SOAP
Manufacturer: The Procter & Gamble Manufacturing Company
Category: otc | Type: HUMAN OTC DRUG LABEL
Date: 20250826

ACTIVE INGREDIENTS: CHLOROXYLENOL 0.3 g/100 mL
INACTIVE INGREDIENTS: TETRASODIUM GLUTAMATE DIACETATE; DECETH-8; ALCOHOL; WATER; SODIUM LAURYL SULFATE; LAURAMINE OXIDE; PHENOXYETHANOL; SODIUM CHLORIDE; PPG-26; FD&C YELLOW NO. 5; D&C RED NO. 33; SODIUM HYDROXIDE; C9-11 PARETH-8

Dawn® Ultra Antibacterial Hand
Orange Scent

Drug Facts

Active ingredient

Chloroxylenol 0.30%

Purpose

Antibacterial hand soap

Use

- for handwashing to decrease bacteria on the skin

Warnings

For external use only

Keep out of reach of children. In case of accidental ingestion, drink a glass of water to dilute. If eye contact occurs, rinse thoroughly with water.

Directions

- wet hands and forearms. Apply 5 ml or palmful to hands and forearms. Scrub thoroughly for 30 sec. and rinse.

Inactive ingredients

Water, sodium lauryl sulfate, lauramine oxide, alcohol denat., phenoxyethanol, tetrasodium glutamate diacetate, sodiumchloride, fragrance, deceth-8, C9-11 alketh-8, PPG-26, sodium hydroxide, yellow 5, red 33

Questions?

1-800-725-3296

Distributed by PROCTER & GAMBLE,
CINCINNATI, OH 45202

PRINCIPAL DISPLAY PANEL - 1.12L (1.18 QT) Bottle Label

DAWN ®
ULTRA

CHLOROXYLENOL ANTIBACTERIAL HAND SOAP

ORANGE SCENT

*VS DAWN NON-CONCENTRATED

DISHWASHING LIQUID

1.12L (1.18 QT) 38 FL OZ